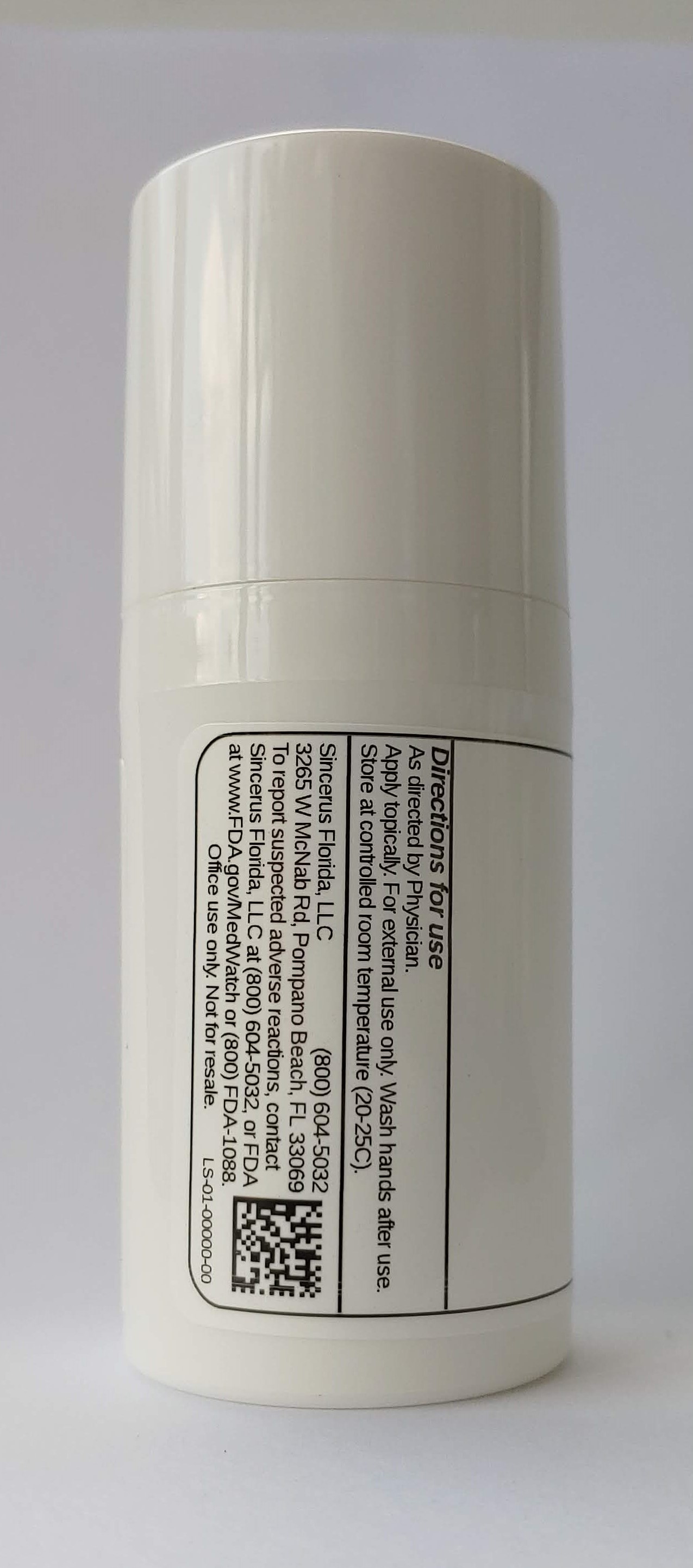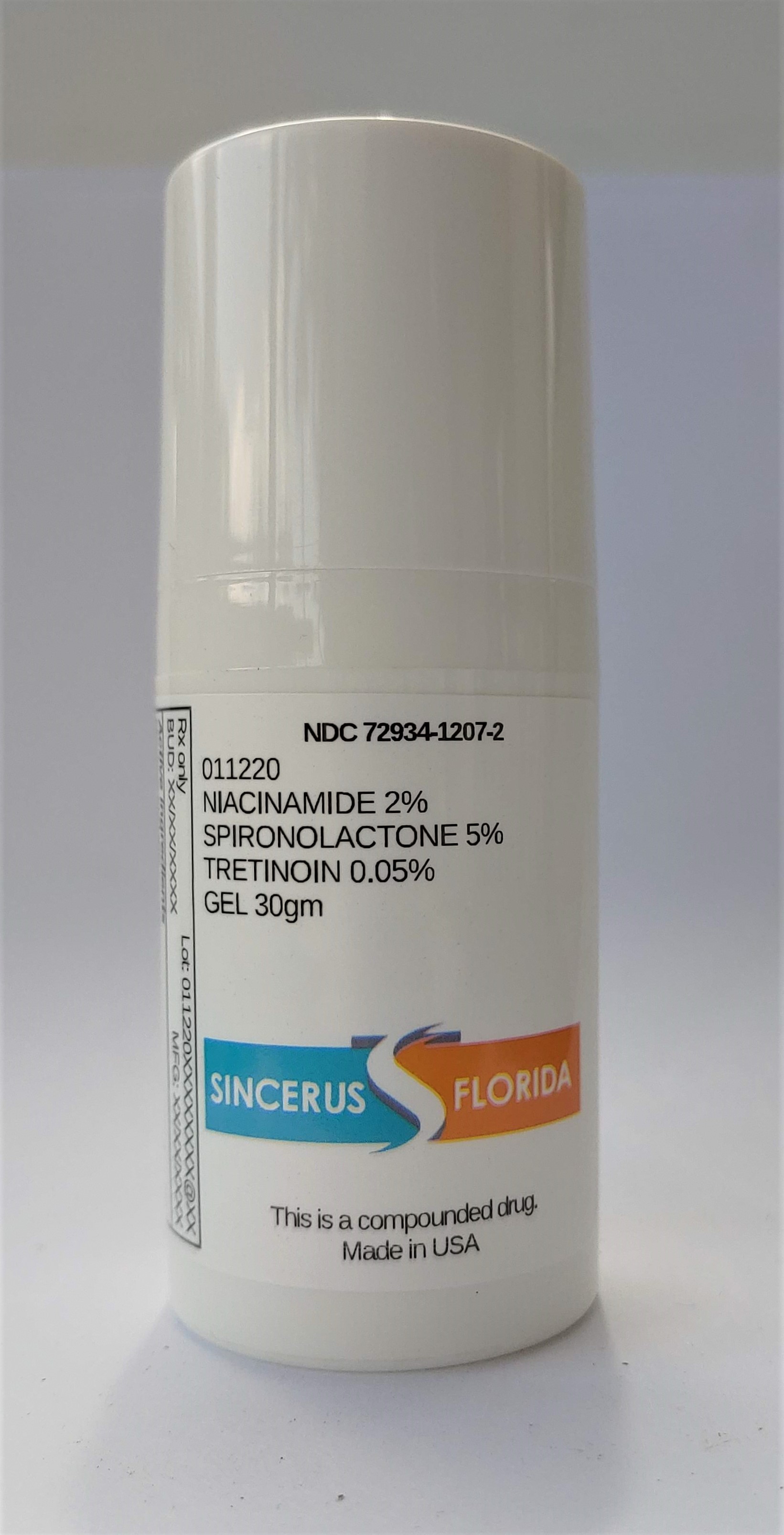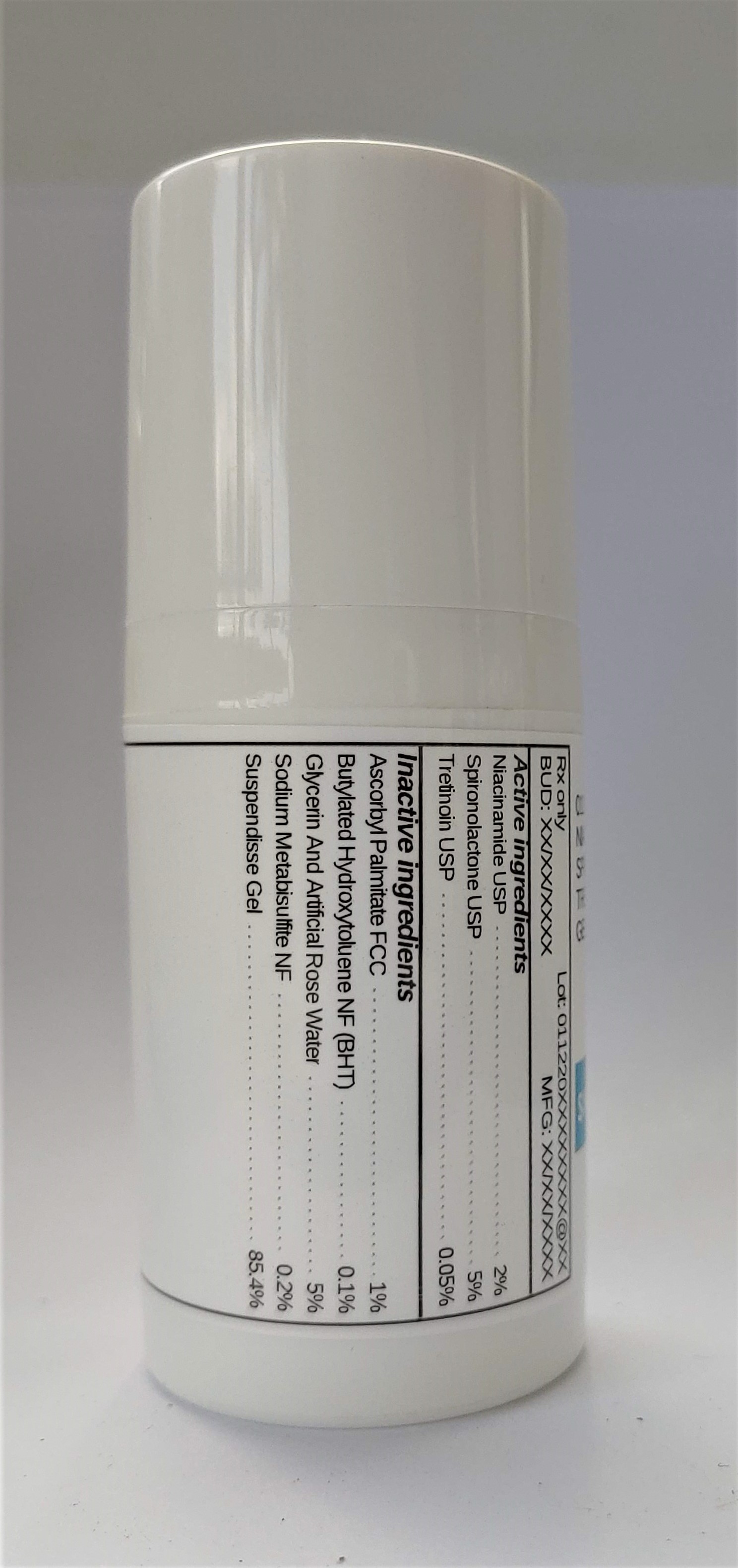 DRUG LABEL: 011220 NIACINAMIDE 2% / SPIRONOLACTONE 5% / TRETINOIN 0.05%
NDC: 72934-1207 | Form: GEL
Manufacturer: Sincerus Florida, LLC
Category: prescription | Type: HUMAN PRESCRIPTION DRUG LABEL
Date: 20200702

ACTIVE INGREDIENTS: SPIRONOLACTONE 5 g/100 g; TRETINOIN 0.05 g/100 g; NIACINAMIDE 2 g/100 g

011220 NIACINAMIDE 2% / SPIRONOLACTONE 5% / TRETINOIN 0.05%